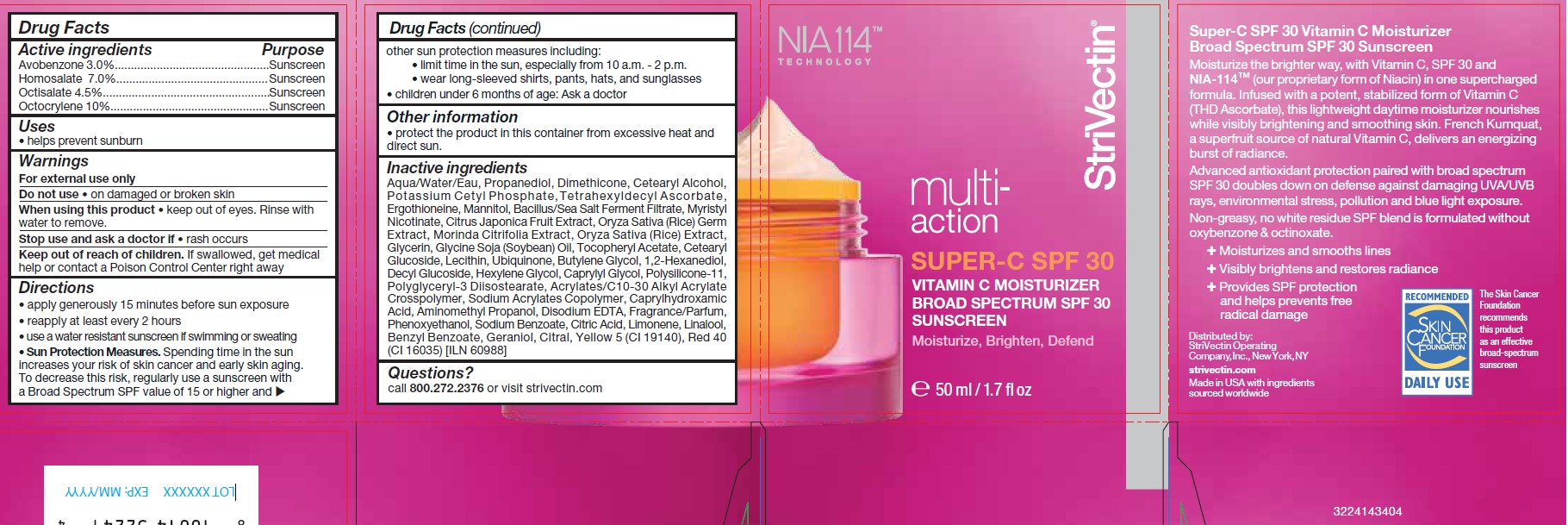 DRUG LABEL: StriVectin multi-action Super-C SPF 30
NDC: 76147-235 | Form: CREAM
Manufacturer: StriVectin Operating Company, Inc.
Category: otc | Type: HUMAN OTC DRUG LABEL
Date: 20251209

ACTIVE INGREDIENTS: AVOBENZONE 3 g/100 mL; HOMOSALATE 7 g/100 mL; OCTISALATE 4.5 g/100 mL; OCTOCRYLENE 10 g/100 mL
INACTIVE INGREDIENTS: WATER; PROPANEDIOL; DIMETHICONE; STEARYL ALCOHOL; CETYL ALCOHOL; POTASSIUM CETYL PHOSPHATE; TETRAHEXYLDECYL ASCORBATE; ERGOTHIONEINE; MANNITOL; SEA SALT; MYRISTYL NICOTINATE; CITRUS JAPONICA FRUIT; RICE GERM; NONI FRUIT; RICE OIL; GLYCERIN; SOYBEAN OIL; .ALPHA.-TOCOPHEROL ACETATE; CETEARYL GLUCOSIDE; LECITHIN, SOYBEAN; UBIQUINOL; BUTYLENE GLYCOL; 1,2-HEXANEDIOL; DECYL GLUCOSIDE; HEXYLENE GLYCOL; CAPRYLYL GLYCOL; POLYSILICONE-15; POLYGLYCERYL-3 DIISOSTEARATE; ACRYLATES CROSSPOLYMER-6; SODIUM ACRYLATE; CAPRYLHYDROXAMIC ACID; AMINOMETHYL PROPANEDIOL; DISODIUM EDTA-COPPER; PHENOXYETHANOL; SODIUM BENZOATE; CITRIC ACID ACETATE; LIMONENE, (+)-; LINALOOL, (+)-; BENZYL BENZOATE; GERANIOL; CITRAL; FD&C YELLOW NO. 5; FD&C RED NO. 40

StriVectin Multi-Action Super-C SPF 30

ACTIVE INGREDIENTS

Avobenzone 3.0%
Homosalate 7.0%
Octisalate 4.5%
Octocrylene 10%

PURPOSE

Sunscreen

USES

- helps prevent sunburn
- if used as directed with other sun protection measures (see Directions), decreases the risk of skin cancer and early skin aging caused by the sun

WARNINGS

- For external use only
- Do not use on damaged or broken skin
- When using this product keep out of eyes. Rinse with water to remove.
- Stop use and ask a doctor if rash occurs

Keep out of reach of children.

If swallowed, get medical help or contact
a Poison Control Center right away.

DIRECTIONS

- Apply generously 15 minutes before sun exposure and as needed
- reapply at least every 2 hours
- use a water resistant sunscreen if swimming or sweating
- Sun Protection Measures. Spending time inthe sun increases your risk of skin cancer andearly skin aging. To decrease this risk, regularly use a sunscreen with a Broad Spectrum SPFvalue of 15 or higher and other sun protectionmeasures including:
- limit time in the sun, especially from 10 a.m. - 2 p.m.
- wear long-sleeved shirts, pants, hats,and sunglasses
- children under 6 months of age: ask a doctor

OTHER INFORMATION

Protect the product in this container from excessive heat and direct sun.

INACTIVE INGREDIENTS

Aqua/Water/Eau, Propanediol, Dimethicone, Cetearyl Alcohol, Potassium Cetyl Phosphate, Tetrahexyldecyl Ascorbate, Ergothioneine, Mannitol, Bacillus/Sea Salt, Ferment Filtrate, Myristyl Nicotinate, Citrus Japonica Fruit Extract, Oryza Sativa (Rice) Germ Extract, Morinda Citrifolia Extract, Oryza Sativa (Rice) Extract, Glycerin,Glycerin Soja (Soybean) Oil, Tocopheryl Acetate, Cetearyl Glucoside, Lecithin, Ubiquinone, Butylene Glycol, 1,2 Hexanediol, Decyl Glucoside, Hexylene Gkycik, CaprylylGlycol, Polysilicon-11, Polyglyceritl-3 Diisostearate, Acrylates/C 10-30Alkyl Acrylate Crosspolymer, Sodium Acrylates Copolymer, Caprylhydroamic Acid, Aminomethyl Propanol, Disodium EDTA, Fragrance/Parfum, Phenoxyethanol, Sodium Benzoate, Citric Acid, Limonene, Linalool, Benzyl Benzoate, Geraniol, Citral, Yellow 5 (CI 19140), Red 40 (CI 16035), [ILN 60988]

Super-C SPF 30 50mL.